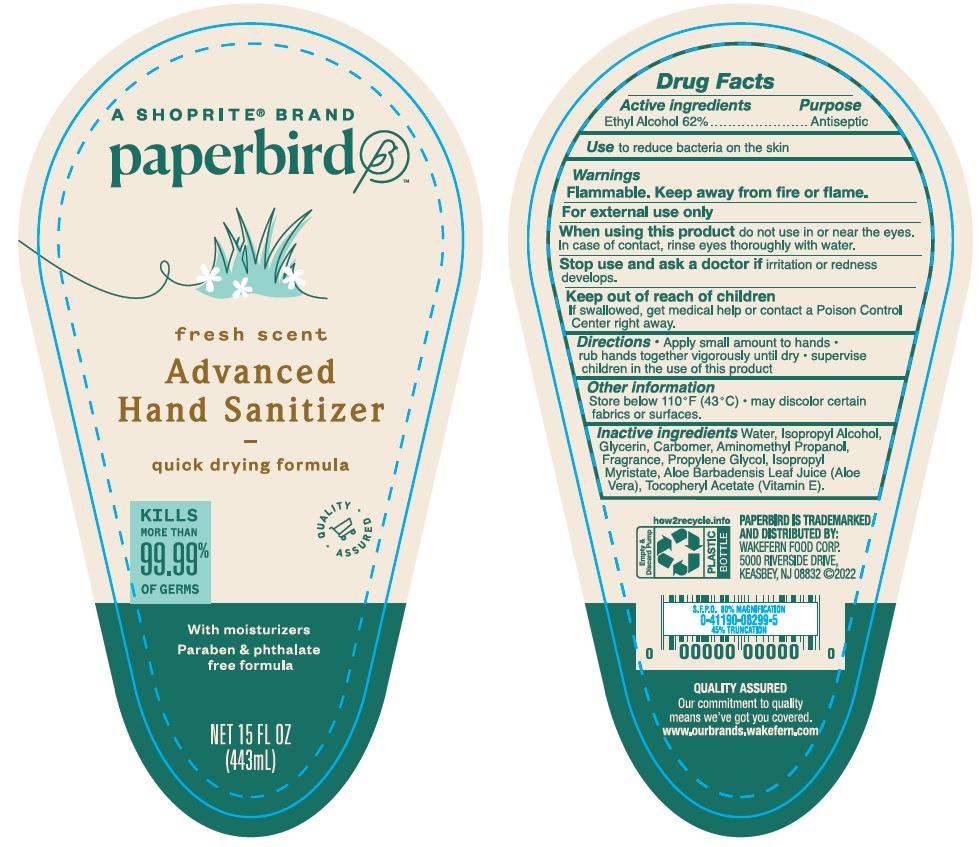 DRUG LABEL: Germ Eliminator
NDC: 42669-015 | Form: LIQUID
Manufacturer: Davion, Inc
Category: otc | Type: HUMAN OTC DRUG LABEL
Date: 20230504

ACTIVE INGREDIENTS: ALCOHOL 62 mL/100 mL
INACTIVE INGREDIENTS: WATER; ISOPROPYL ALCOHOL; GLYCERIN; CARBOMER HOMOPOLYMER, UNSPECIFIED TYPE; AMINOMETHYLPROPANOL; PROPYLENE GLYCOL; ISOPROPYL MYRISTATE; ALOE VERA LEAF; .ALPHA.-TOCOPHEROL ACETATE

Drug Facts

Active Ingredient

Ethyl Alcohol 62%

Purpose

Antiseptic

Use

To reduce bacteria on the skin

WARNINGS

Flammable, Keep away from fire or flame.

For external use only.

When using this product

do not use in or near the eyes. In case of contact, rinse eyes thoroughly with water

Stop use and ask a doctor if

irritation or redness develops

Keep out of reach of children

If swallowed, get medical help or contact a Poison Control Center right away.

Directions

- Apply small amount to hands
- rub hands together vigorously until dry
- supervise children in use of this product

Other information

Store below 110°F (43° C)

may discolor certain fabrics or surfaces

Inactive Ingredients

Water, Isopropyl Alcohol, Glycerin, Carbomer, Aminomethyl Propanol, Fragrance, Propylene Glycol, Isopropyl Myristate, Aloe Barbadensis Leaf Juice (Aloe Vera), Tocopheryl Acetate (Vitamin E).

Principal Display Panel

A SHOPRITE BRAND

paperbird

fresh scent

Advanced

Hand Sanitizer

quick drying formula

KILLS

MORE THAN

99.99%

OF GERMS

With moisturizers

Paraben & phthalate

free formula

NET 15 FL OZ

(443 mL)